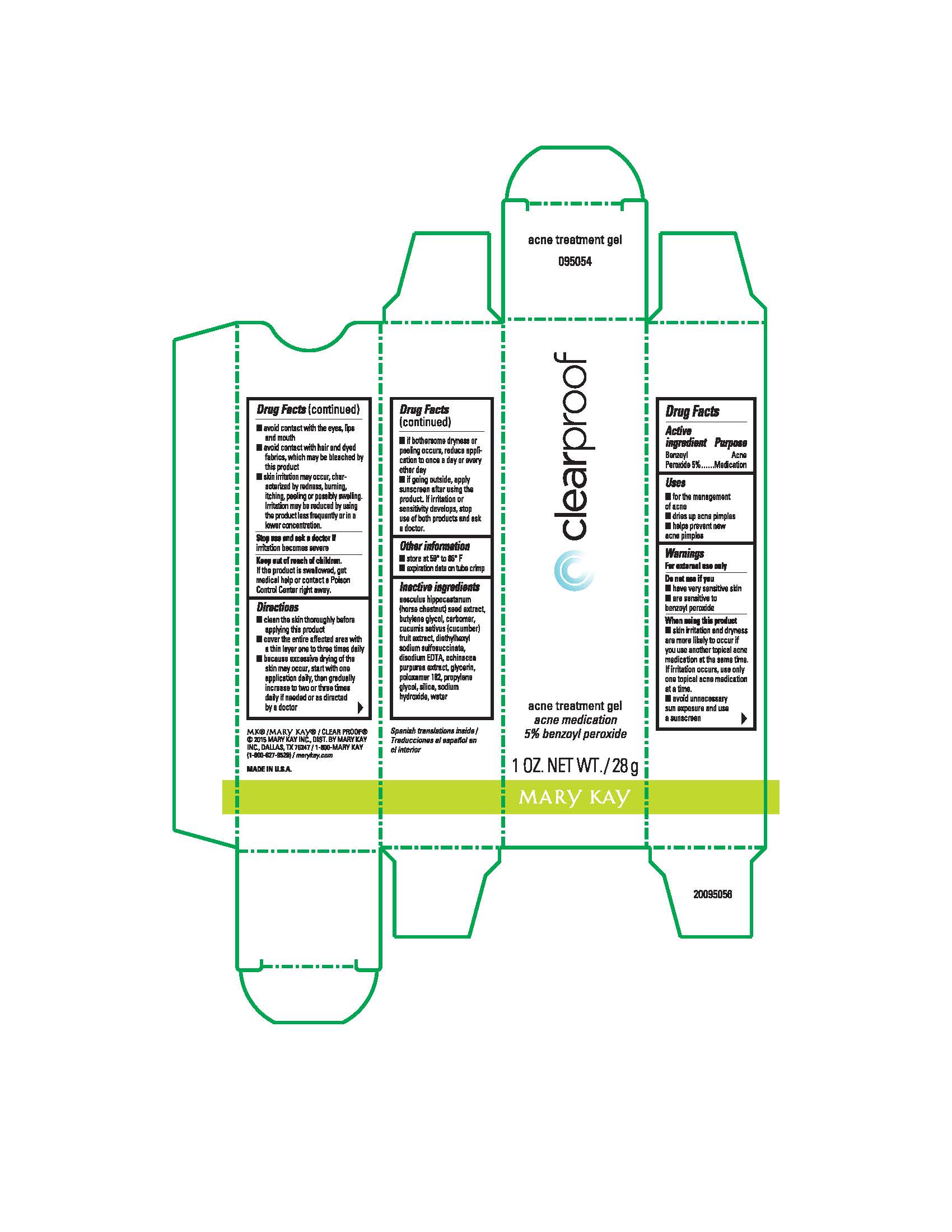 DRUG LABEL: Clear Proof Acne Treatment
NDC: 51531-9071 | Form: GEL
Manufacturer: Mary Kay Inc.
Category: otc | Type: HUMAN OTC DRUG LABEL
Date: 20241217

ACTIVE INGREDIENTS: BENZOYL PEROXIDE 5 g/100 g
INACTIVE INGREDIENTS: WATER; PROPYLENE GLYCOL; POLOXAMER 182; SILICON DIOXIDE; CARBOMER HOMOPOLYMER TYPE C (ALLYL PENTAERYTHRITOL CROSSLINKED); SODIUM HYDROXIDE; DOCUSATE SODIUM; EDETATE DISODIUM; GLYCERIN; BUTYLENE GLYCOL; ECHINACEA PURPUREA; CUCUMBER; HORSE CHESTNUT

Clear Proof Acne Treatment Gel
Drug Facts

Active ingredient:

Benzoyl Peroxide 5%

Purpose

Acne Medication

Uses

- for the management of acne
- dries up acne pimples
- helps prevent new acne pimples

Warnings

For external use only.

Do not use if you

- have very sensitive skin
- are sensitive to benzoyl peroxide

When using this product

- skin irritation and dryness is more likely to occur if you use another topical acne medication at the same time. If irritation occurs, only use one topical acne medication at a time.
- avoid unnecessary sun exposure and use a sunscreen
- avoid contact with the eyes, lips and mouth
- avoid contact with hair and dyed fabrics, which may be bleached by this product
- skin irritation may occur, characterized by redness, burning, itching, peeling or possibly swelling. Irritation may be reduced by using the product less frequently or in a lower concentration.

Stop use and ask a doctor if

irritation becomes severe

Keep out of reach of children.

If swallowed, get medical help or contact a Poison Control Center right away.

Directions

- clean the skin thoroughly before applying this product
- cover the entire affected area with a thin layer one to three times daily
- because excessive drying of the skin may occur, start with one application daily, then gradually increase to two or three times daily if needed or as directed by a doctor
- if bothersome dryness or peeling occurs, reduce application to once a day or every other day
- if going outside, apply sunscreen after using this product. If irritation or sensitivity develops, stop use of both products and ask a doctor.

Other information

- store at 59° to 86° F
- expiration date on tube crimp

Inactive ingredients

aesculus hippocastanum (horse chestnut) seed extract, butylene glycol, carbomer, cucumis sativus (cucumber) fruit extract, diethylhexyl sodium sulfosuccinate, disodium EDTA, echinacea purpurea extract, glycerin, poloxamer 182, propylene glycol, silica, sodium hydroxide, water

Principal Display Panel - 28 g carton

clearproof

acne treatment gel

acne medication
5% benzoyl peroxide

1 OZ. NET WT./28 g

Mary Kay